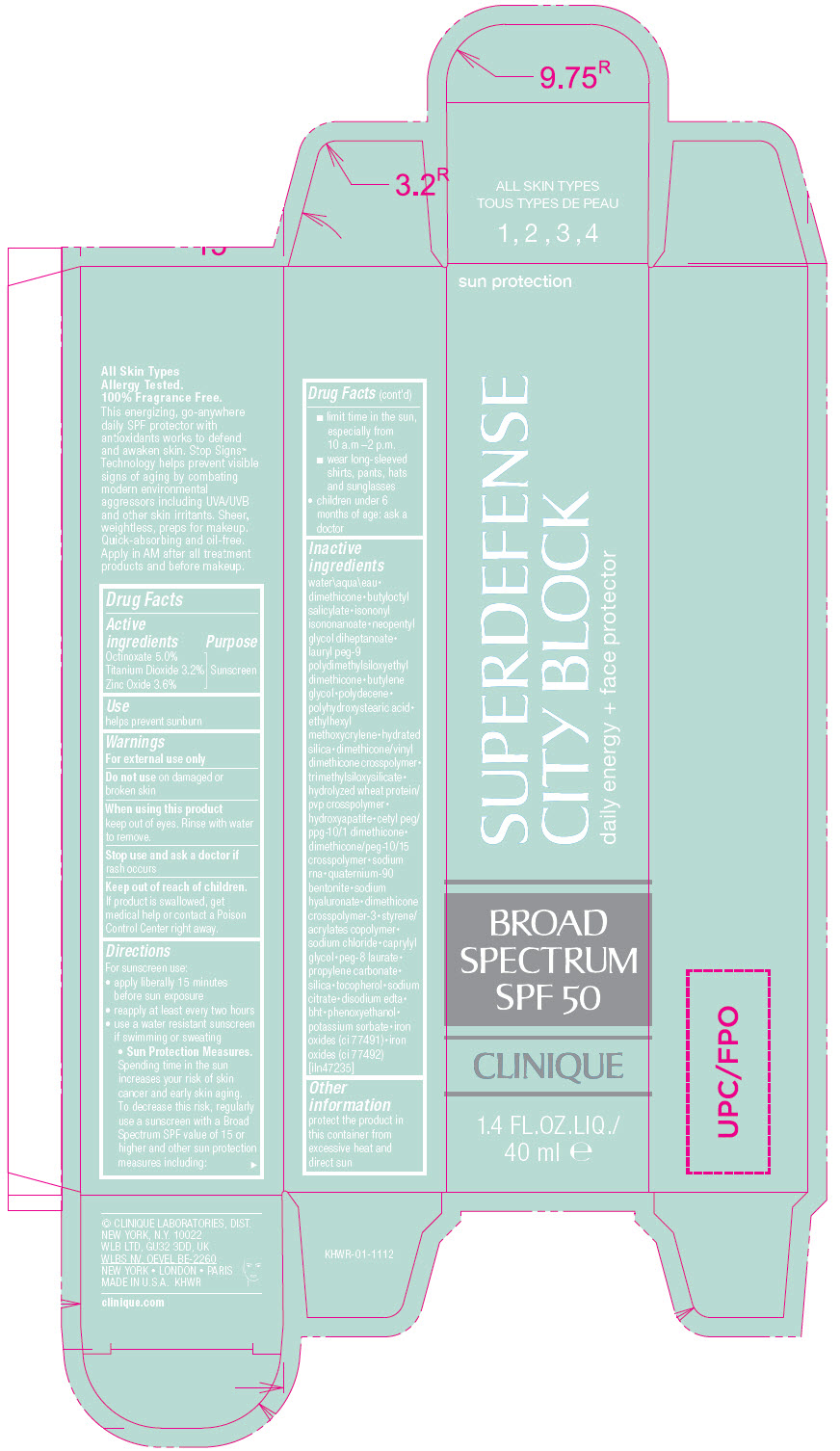 DRUG LABEL: CLINIQUE SUPER DEFENSE CITY BLOCK DAILY ENERGY PLUS FACE PROTECTOR BROAD SPECTRUM SPF 50
NDC: 49527-078 | Form: LOTION
Manufacturer: CLINIQUE LABORATORIES LLC
Category: otc | Type: HUMAN OTC DRUG LABEL
Date: 20241225

ACTIVE INGREDIENTS: OCTINOXATE 50 mg/1 mL; TITANIUM DIOXIDE 32 mg/1 mL; ZINC OXIDE 36 mg/1 mL
INACTIVE INGREDIENTS: WATER; DIMETHICONE 100; BUTYLOCTYL SALICYLATE; ISONONYL ISONONANOATE; NEOPENTYL GLYCOL DIHEPTANOATE; LAURYL PEG-9 POLYDIMETHYLSILOXYETHYL DIMETHICONE; 1,2-BUTANEDIOL; HYDROGENATED DIDECENE; POLYHYDROXYSTEARIC ACID (2300 MW); ETHYLHEXYL METHOXYCRYLENE; HYDRATED SILICA; DIMETHICONE/VINYL DIMETHICONE CROSSPOLYMER (HARD PARTICLE); TRIMETHYLSILOXYSILICATE (M/Q 0.6-0.8); HYDROLYZED WHEAT PROTEIN (ENZYMATIC; 3000 MW); TRIBASIC CALCIUM PHOSPHATE; CETYL PEG/PPG-10/1 DIMETHICONE (HLB 2); BIS-PEG-10 DIMETHICONE/DIMER DILINOLEATE COPOLYMER; SODIUM CARBONATE; BENTONITE; HYALURONATE SODIUM; DIMETHICONE CROSSPOLYMER (450000 MPA.S AT 12% IN CYCLOPENTASILOXANE); METHACRYLATE/METHOXY PEG-10 MALEATE/STYRENE COPOLYMER; SODIUM CHLORIDE; CAPRYLYL GLYCOL; PEG-8 LAURATE; PROPYLENE CARBONATE; SILICON DIOXIDE; TOCOPHEROL; SODIUM CITRATE, UNSPECIFIED FORM; EDETATE DISODIUM ANHYDROUS; BUTYLATED HYDROXYTOLUENE; PHENOXYETHANOL; POTASSIUM SORBATE; FERRIC OXIDE RED

CLINIQUE SUPER DEFENSE CITY BLOCK DAILY ENERGY + FACE PROTECTOR BROAD SPECTRUM SPF 50

Drug Facts

Active ingredients

Octinoxate 5.0%
Titanium Dioxide 3.2%
Zinc Oxide 3.6%

Purpose

Sunscreen

Use

helps prevent sunburn

Warnings

For external use only

Do not use on damaged or broken skin

When using this product keep out of eyes. Rinse with water to remove.

Stop use and ask a doctor if rash occurs

Keep out of reach of children. If product is swallowed, get medical help or contact a Poison Control Center right away.

Directions

For sunscreen use:

- apply liberally 15 minutes before sun exposure
- reapply at least every two hours
- use a water resistant sunscreen if swimming or sweating
  - Sun Protection Measures. Spending time in the sun increases your risk of skin cancer and early skin aging. To decrease this risk, regularly use a sunscreen with a Broad Spectrum SPF value of 15 or higher and other sun protection measures including:
    - limit time in the sun, especially from 10 a.m –2 p.m.
    - wear long-sleeved shirts, pants, hats and sunglasses
- children under 6 months of age: ask a doctor

Inactive ingredients

water\aqua\eau•dimethicone•butyloctyl salicylate•isononyl isononanoate•neopentyl glycol diheptanoate•lauryl peg-9 polydimethylsiloxyethyl dimethicone•butylene glycol•polydecene•polyhydroxystearic acid•ethylhexyl methoxycrylene•hydrated silica•dimethicone/vinyl dimethicone crosspolymer•trimethylsiloxysilicate•hydrolyzed wheat protein/pvp crosspolymer•hydroxyapatite•cetyl peg/ppg-10/1 dimethicone•dimethicone/peg-10/15 crosspolymer•sodium rna•quaternium-90 bentonite•sodium hyaluronate•dimethicone crosspolymer-3•styrene/acrylates copolymer•sodium chloride•caprylyl glycol•peg-8 laurate•propylene carbonate•silica•tocopherol•sodium citrate•disodium edta•bht•phenoxyethanol•potassium sorbate•iron oxides (ci 77491)•iron oxides (ci 77492) [iln47235]

Other information

protect the product in this container from excessive heat and direct sun

PRINCIPAL DISPLAY PANEL - 40 ml Tube Carton

sun protection

SUPERDEFENSE
CITY BLOCK

daily energy + face protector

BROAD
SPECTRUM
SPF 50

CLINIQUE

1.4 FL.OZ.LIQ./
40 ml e